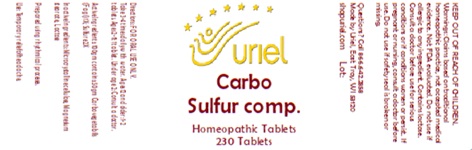 DRUG LABEL: Carbo Sulfur comp.
NDC: 48951-3282 | Form: TABLET
Manufacturer: Uriel Pharmacy, Inc
Category: homeopathic | Type: HUMAN OTC DRUG LABEL
Date: 20250311

ACTIVE INGREDIENTS: CHARCOAL POWDER 1 [hp_X]/1 1; SULFUR 2 [hp_X]/1 1
INACTIVE INGREDIENTS: MAGNESIUM STEARATE; MICROCRYSTALLINE CELLULOSE; LACTOSE

Carbo Sulfur comp.

INDICATIONS AND USAGE

Directions: FOR ORAL USE ONLY.

DOSAGE AND ADMINISTRATION

Take 3-4 times daily with water. Ages 12 and older: 1-2 tablets. Ages 2-11: 1 tablet. Under age 2: Consult a doctor.

ACTIVE INGREDIENT

Active Ingredients: 100gm contains: 50gm Carbo vegetabilis (Fagi) 1X; Sulfure 2X

INACTIVE INGREDIENT

Inactive Ingredients: Microcrystalline cellulose, Magnesium stearate, Lactose

Prepared using rhythmical processes.

PURPOSE

Use: Temporary relief of headache.

KEEP OUT OF REACH OF CHILDREN.

WARNINGS

Warnings: Claims based on traditional homeopathic practice, not accepted medical evidence. Not FDA evaluated. Do not use if allergic to any ingredient. Contains lactose. Consult a doctor before use for serious conditions or if conditions worsen or persist. If pregnant or nursing, consult a doctor before use. Do not use if safety seal is broken or missing.

Questions? Call 866.642.2858
Made by Uriel, East Troy, WI 53120
shopuriel.com Lot: